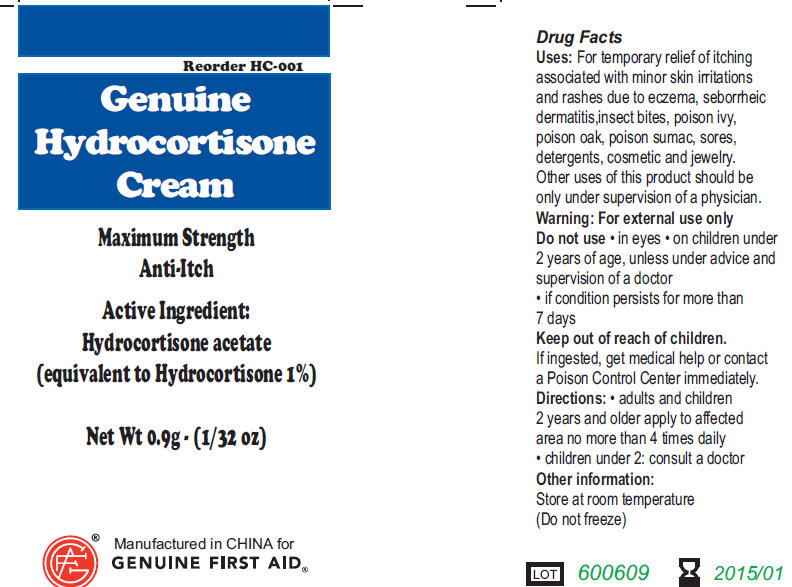 DRUG LABEL: Hydrocortisone
NDC: 52124-0007 | Form: CREAM
Manufacturer: Genuine First Aid
Category: otc | Type: HUMAN OTC DRUG LABEL
Date: 20111201

ACTIVE INGREDIENTS: HYDROCORTISONE ACETATE 1 g/100 g
INACTIVE INGREDIENTS: PROPYLENE GLYCOL; WATER

Genuine Hydrocortisone Cream Maximum Strength Anti-Itch

Active Ingredient

Hydrocortisone acetate (equivalent to Hydrocortisone 1%)

Purpose

Maximum strength Anti-itch

Uses

For temporary relief of itching associated with minor skin irritations and rashes due to eczema, seborrheic dermatitis, insect bites, poison ivy, poison oak, poison sumac, sores, detergents, cosmetic and jewelry. Other uses of this product should be only under supervision of a physician.

Warnings

For external use only.

Do not use:

In eyes. On children under 2 years of age, unless under advice and supervision of a doctor.

If condition persists for more than 7 days.

Keep out of reach of children

If ingested, get medical help or contact a Poison Control Center immediately.

Directions

Adults and Children 2 years and older apply to affected area no more than 4 times daily,

Children under 2: Consult a doctor

Other Information

Store at room temperature

(Do not freeze)

Inactive Ingredients

Propylene glycol, Carbomer, Purified water.

PACKAGE LABEL

Genuine Hydrocortisone Cream
Maximum Strength
Anti-Itch
Net Wt 0.9g (1/32 oz)
Manufactured in CHINA for
Genuine First Aid